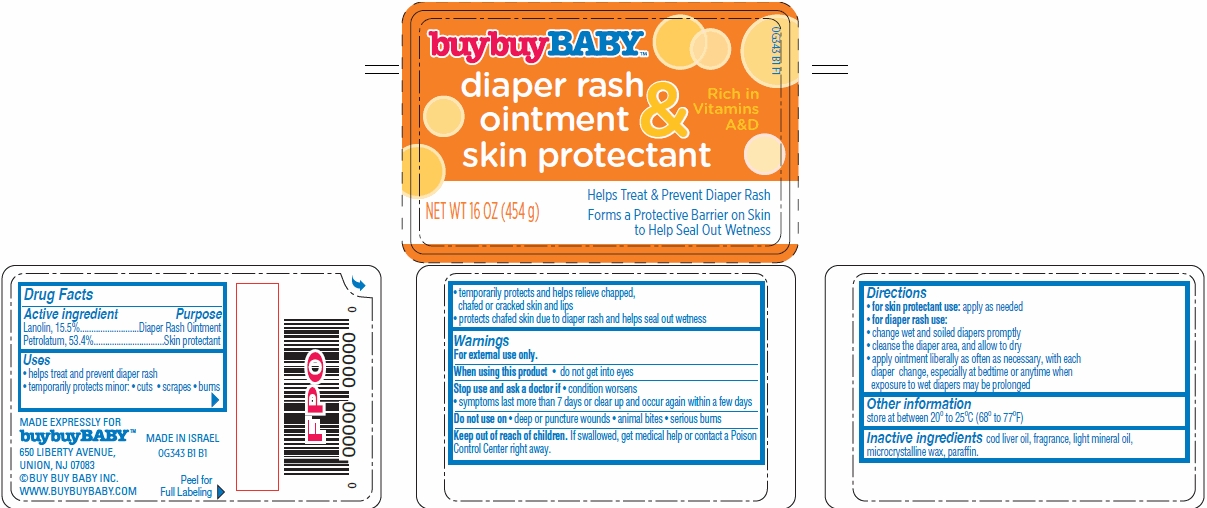 DRUG LABEL: A D and L Original Diaper Rash Skin
NDC: 63940-343 | Form: OINTMENT
Manufacturer: Harmon Stores Inc.
Category: otc | Type: HUMAN OTC DRUG LABEL
Date: 20140912

ACTIVE INGREDIENTS: LANOLIN 15.5 g/100 g; PETROLATUM 53.4 g/100 g
INACTIVE INGREDIENTS: COD LIVER OIL; MICROCRYSTALLINE WAX; PARAFFIN; LIGHT MINERAL OIL

buybuyBaby™ diaper rash ointment and skin protectant

Active ingredient

Lanolin, 15.5%
Petrolatum, 53.4%

Purpose

Diaper Rash Ointment
Skin protectant

Uses

- helps treat and prevent diaper rash
- temporarily protects minor:
  - cuts
  - scrapes
  - burns
- temporarily protects and helps relieve chapped, chafed or cracked skin and lips
- protects chafed skin due to diaper rash and helps seal out wetness

Warnings

For external use only.

When using this product

- do not get into eyes

Stop use and ask a doctor if

- condition worsens
- symptoms last more than 7 days or clear up and occur again within a few days

Do not use on

- deep or puncture wounds
- animal bites
- serious burns

Keep Out of Reach of Children

If swallowed, get medical help or contact a Poison Control Center right away.

Directions

- for skin protectant use: apply as needed
- for diaper rash use:
- change wet and soiled diapers promptly
- cleanse the diaper area, and allow to dry
- apply ointment liberally as often as necessary, with each diaper change, especially at bedtime or anytime when exposure to wet diapers may be prolonged

Other information

store at between 20° to 25°C (68° to 77°F)

Inactive ingredients

cod liver oil, fragrance, light mineral oil, microcrystalline wax, paraffin.

Package/Label Principal Display Panel

buybuyBABYTM

diaper rash
ointment &
skin protectant

Rich in
Vitamins
A&D

Helps Treat & Prevent Diaper Rash
Forms a Protective Barrier on Skin
to Help Seal Out Wetness

NET WT 16 OZ (454 g)

MADE EXPRESSLY FOR
buybuyBABY™
650 LIBERTY AVENUE,
UNION, NJ 07083
©BUY BUY BABY INC.
WWW.BUYBUYBABY.COM

MADE IN ISRAEL
0G343 B1 B1

Peel for
Full Labeling

Carton Label